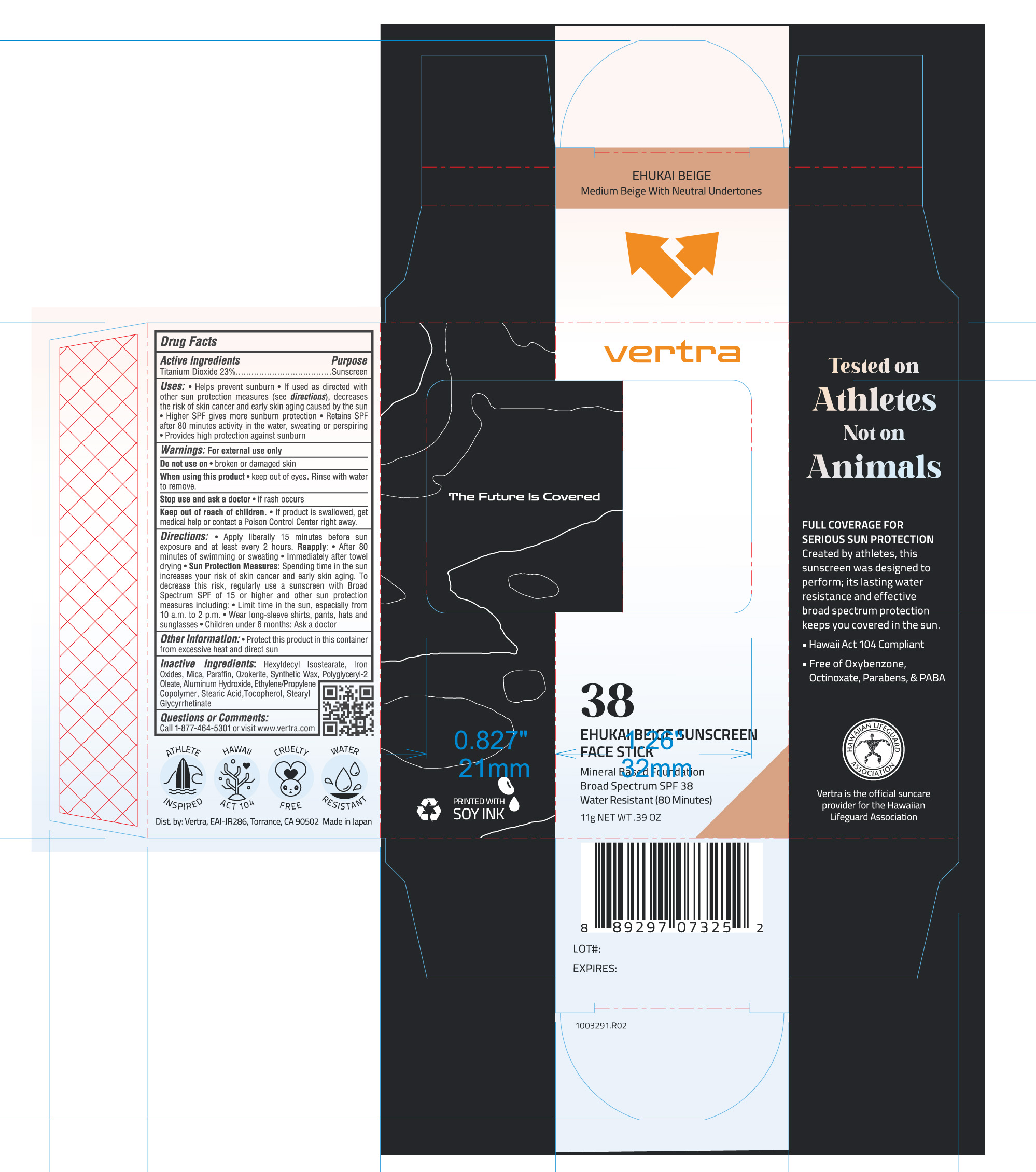 DRUG LABEL: Vertra Ehukai Beige Face Stick SPF 38
NDC: 66990-1020 | Form: STICK
Manufacturer: Toshiki Pigment Co., ltd.
Category: otc | Type: HUMAN OTC DRUG LABEL
Date: 20251104

ACTIVE INGREDIENTS: TITANIUM DIOXIDE 23 g/100 g
INACTIVE INGREDIENTS: FERRIC OXIDE RED; FERROSOFERRIC OXIDE; MICA; PARAFFIN; STEARYL GLYCYRRHETINATE; HEXYLDECYL ISOSTEARATE; ALUMINUM HYDROXIDE; TOCOPHEROL; FERRIC OXIDE YELLOW; STEARIC ACID; SYNTHETIC WAX (1200 MW); POLYGLYCERYL-2 OLEATE; CERESIN

Vertra Ehukai Beige Face Stick SPF 38

Active Ingredients Purpose

TITANIUM DIOXIDE 23% Sunscreen

Uses

- Helps prevent sunburn.
- If used as directed with other sun protection measures (see directions), decreases the risk of skin cancer and early skin aging caused by the sun
- Higher SPF gives more sunburn protection.
- Retains SPF after 80 minutes activity in the water, sweating, or perspiring
- Provides high protection against sunburn

Keep out of reach of children:

- If product is swallowed, get medical help or contact a Poison Control Center right away.

Stop use and ask a doctor if:

- Rash or irritation develops and lasts

Warnings

Do not use:

- On damaged or broken skin

When using this product:

- Keep out of eyes. Rinse with water to remove.

For external use only

Directions

- Apply liberally and generously 15 minutes before sun exposure and at least every 2 hours and at least every 2 hours.

Sun Protection Measures Spending time in the sun increases your risk of skin cancer and early skin aging. To decrease this risk, regularly use a sunscreen with a Broad-Spectrum SPF value of 15 or higher and other sun
protection measures including:

• limit your time in the sun, especially from 10 a.m. – 2 p.m.

• wear long-sleeved shirts, pants, hats, and sunglasses

•Children under 6 months of age: ask a doctor

Reapply:

- After 80 minutes of swimming or sweating
- Immediately after towel drying
- At least every 2 hours

Inactive Ingredients

Hexyldecyl Isostearate, Aluminum Hydroxide, Mica, Iron Oxides, Stearic Acid, Paraffin, Ozokerite, Synthetic Wax, Ethylene/Propylene Copolymer, Polyglyceryl-2 Oleate, Tocopherol, Stearyl Glycyrrhetinate

PACKAGE LABEL

Vertra

38

Ehukai Beige Face Stick

Mineral Based Foundation

Broad Spectrum SPF 38

Water Resistant (80 minutes)

11g NET WT. 0.39 OZ